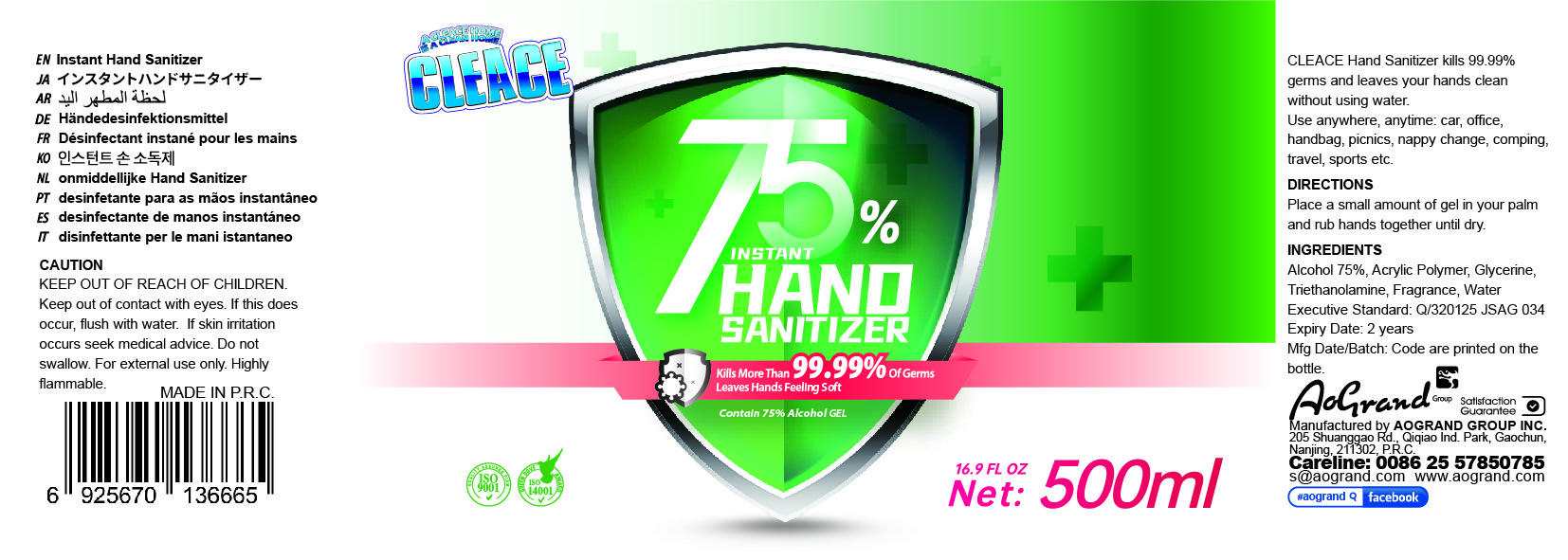 DRUG LABEL: 75% alcohol hand sanitizer
NDC: 74621-001 | Form: GEL
Manufacturer: Aogrand International Trade Corporation
Category: otc | Type: HUMAN OTC DRUG LABEL
Date: 20230211

ACTIVE INGREDIENTS: ALCOHOL 75 mL/100 mL
INACTIVE INGREDIENTS: GLYCERIN; CARBOMER 940; WATER; TROLAMINE

75% alcohol hand sanitizer

Active Ingredient(s)

Alcohol 75% v/v. Purpose: Antiseptic

Purpose

Antiseptic, Hand Sanitizer

Inactive ingredients

Acrylic polymer, Glycerin, Triethanolamine, Water

Directions

- Place a small amount of gel in your palm, and rub hands together until dry.

Warnings

For external use only. Highly flammable.

Do not use

- Do not swallow.

Keep out of reach of children.

STOP USE

If skin irritation occurs seek medical advice.

WHEN USING

Kepp our of contact with eyes. If this does occur, flush with water.

INDICATIONS AND USAGE

Hand Sannitizer kills 99.99% gems and leaves your hand clean without using water

Package Label - Principal Display Panel

500 mL NDC: 74621-001-01